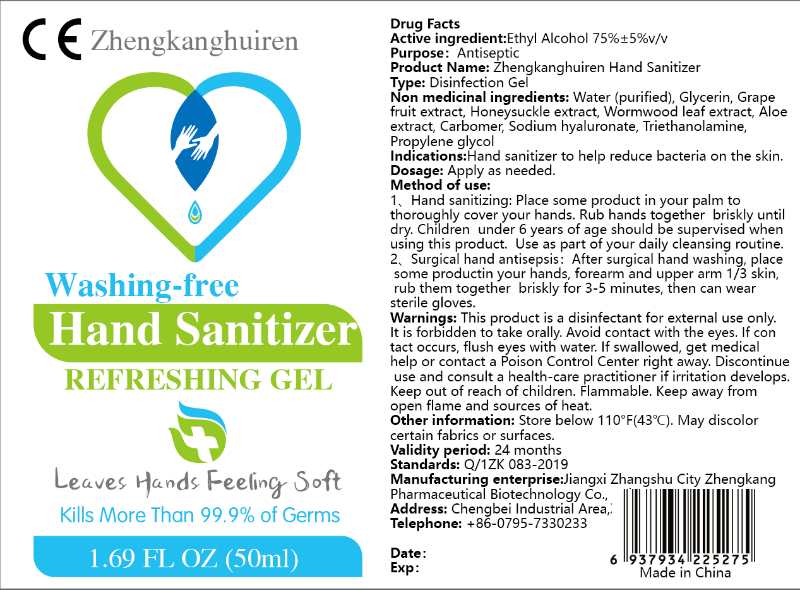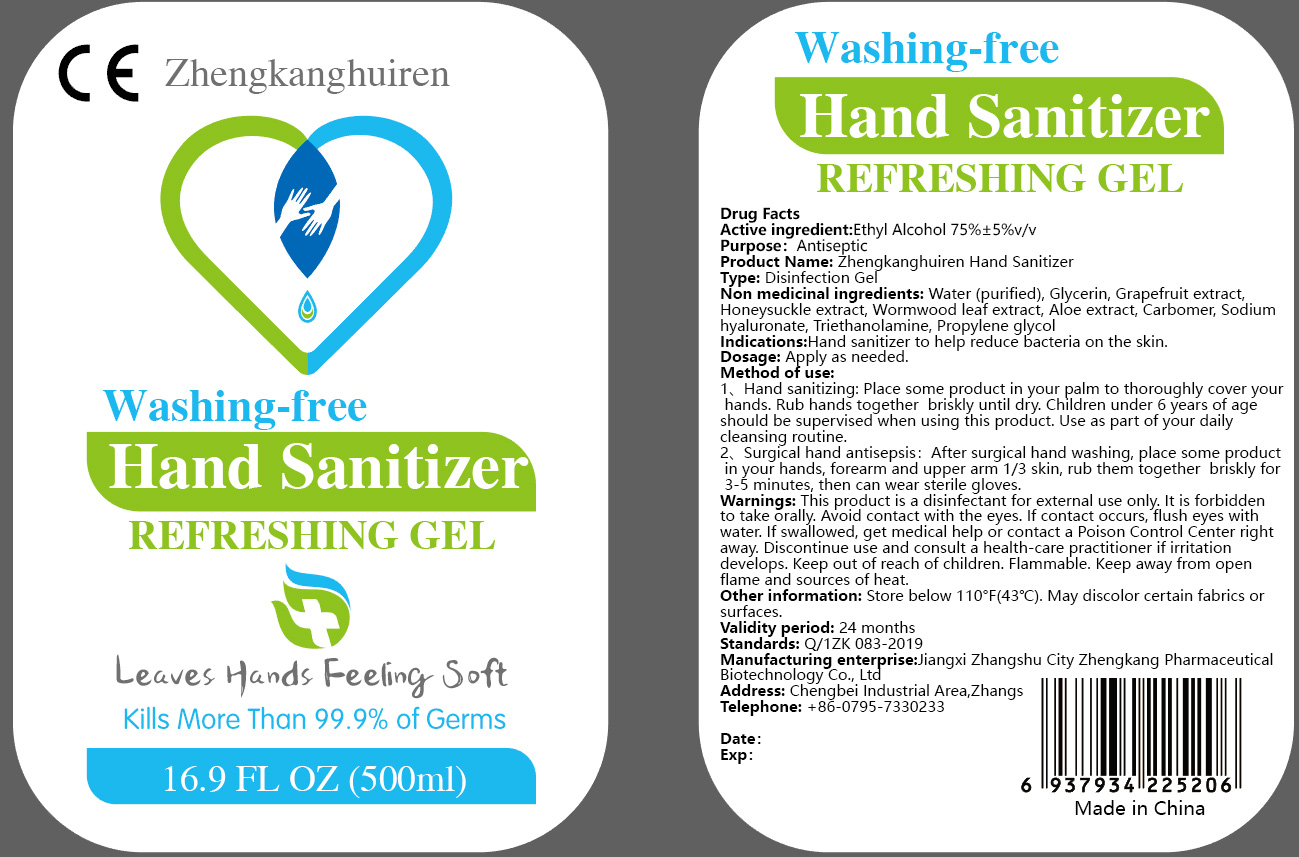 DRUG LABEL: Washing-free Hand Sanitizer
NDC: 74916-001 | Form: GEL
Manufacturer: Jiangxi Zhangshu Zhengkang Medicine Biotechnology Co.,ltd.
Category: otc | Type: HUMAN OTC DRUG LABEL
Date: 20200409

ACTIVE INGREDIENTS: ALCOHOL 75 mL/100 mL
INACTIVE INGREDIENTS: ALOE; WORMWOOD; TROLAMINE; CARBOMER INTERPOLYMER TYPE A (ALLYL SUCROSE CROSSLINKED); PROPYLENE GLYCOL; GLYCERIN 1.45 mL/100 mL; GRAPEFRUIT; WATER; LONICERA JAPONICA FLOWER; PEG-9 DIGLYCIDYL ETHER/SODIUM HYALURONATE CROSSPOLYMER

Washing-free Hand Sanitizer Refereshing gel

Active Ingredient(s)

Alcohol 70% v/v. Purpose: Antiseptic

Purpose

Antiseptic, Hand Sanitizer

Use

Hand Sanitizer to help reduce bacteria on the skin

Warnings

This product is a disinfectant for external use only. Flammable. Keep away from open flame and source of heat

Do not use

It is forbidden to take orally

WHEN USING

Avoid contact with the eyes. If contact occurs, flush eyes with water.

STOP USE

Discontinue use and consult a health-care practitioner if irritation develops.

Keep out of reach of children. If swallowed, get medical help or contact a Poison Control Center right away.

Directions

1. Hand sanitizing: Place some product in your palm to thoroughly cover your hands. Rub hands together briskly until dry. Chirldren under 6 years of age should be supervised when using this product. Use a part of your daily cleansing routine.

2. Surgical hand antisepsis: After surgical hand washing, place some product in your hands, forearm and upper arm 1/3 skin, rub them together briskly for 3-5 minutes, then can wear sterile golves.

Other information

- Store below 110F (43C).
- May discolor certain fabrics or surfaces

Inactive ingredients

Water (purified), Glycerin, Grape fruit extract, Honeysuckle extract, wormwood leaf extract, Aloe extract, Carbomer, Sodium hyaluronate, Triethanolamine, Propylene glycol

Package Label - Principal Display Panel

50 mL NDC: 74621-001-01

500 mL NDC: 74621-001-02